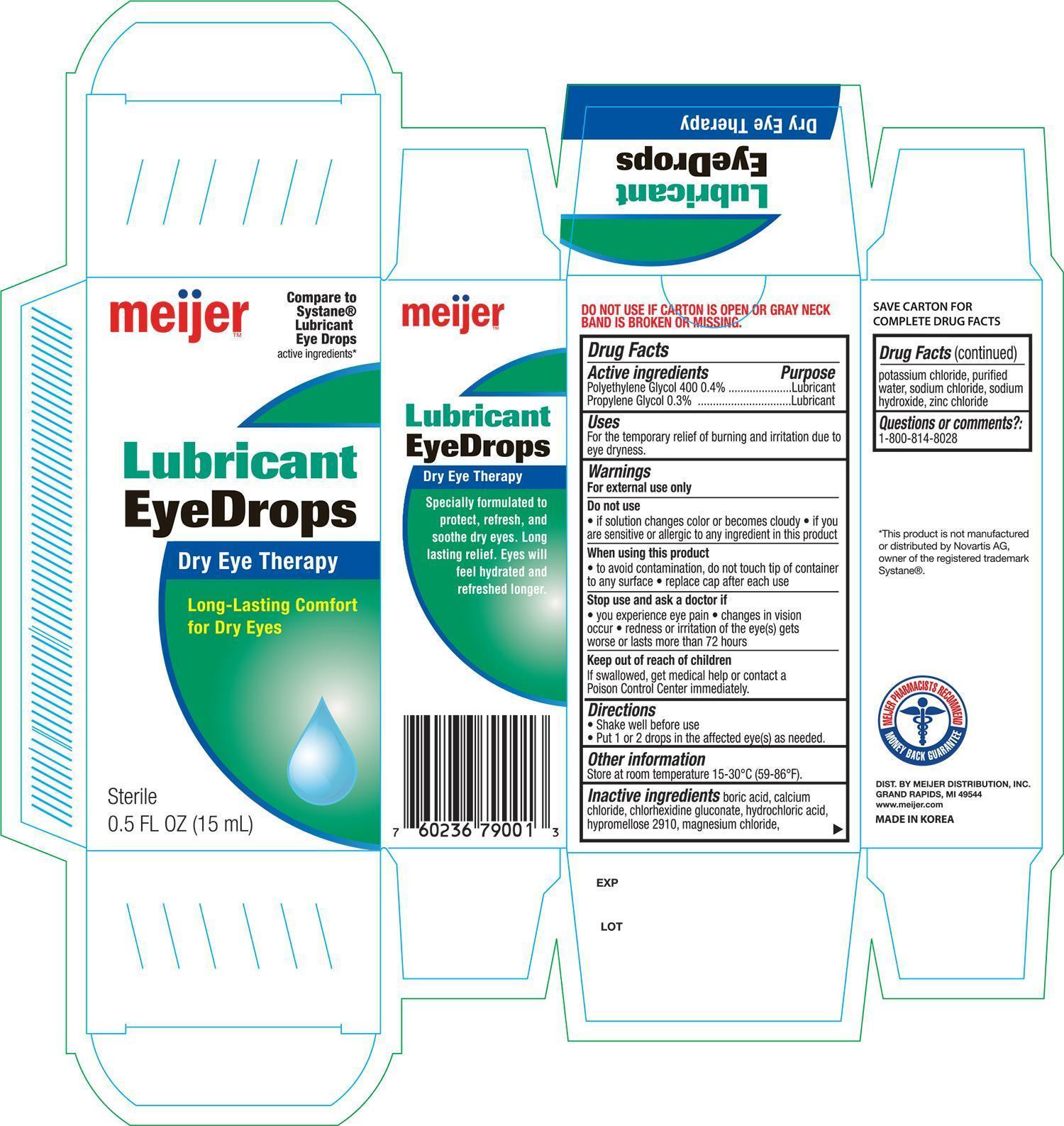 DRUG LABEL: Meijer Lubricant Dry Eye
NDC: 41250-791 | Form: SOLUTION/ DROPS
Manufacturer: Meijer, Inc.
Category: otc | Type: HUMAN OTC DRUG LABEL
Date: 20150106

ACTIVE INGREDIENTS: POLYETHYLENE GLYCOL 400 4 mg/1 mL; PROPYLENE GLYCOL 3 mg/1 mL
INACTIVE INGREDIENTS: BORIC ACID; CALCIUM CHLORIDE; CHLORHEXIDINE GLUCONATE; HYDROCHLORIC ACID; HYPROMELLOSE 2910 (15 MPA.S); MAGNESIUM CHLORIDE; POTASSIUM CHLORIDE; WATER; SODIUM CHLORIDE; SODIUM HYDROXIDE; ZINC CHLORIDE

Active ingredients Purpose

Polyethylene Glycol 400 0.4%............................... Lubricant

Propylene Glycol 0.3%......................................... Lubricant

Uses

For the temporary relief of burning and irritation due to eye dryness

Warnings

For external use only

Do not use

- if solution changes color or becomes cloudy
- if you are sensitive or allergic to any ingredient in this product

When using this product

- to avoid contamination, do not touch tip of container to any surface
- replace cap after each use

Stop use and ask a doctor if

- you experience eye pain
- changes in vision occur
- redness or irritation of the eye(s) gets worse or lasts more than 72 hours

Keep out of reach of children

If swallowed, get medical help or contact a Posion Control Center immediately

Directions

- Shake well before use
- Put 1 or 2 drops in the affected eye(s) as needed

Other information

Store at room temperature 15-30°C (59-86°F)

Inactive ingredients

boric acid, calcium chloride, chlorhexidine gluconate, hydrochloric acid, hypromellose 2910, magnesium chloride, potassium chloride, purified water, sodium chloride, sodium hydroxide, zinc chloride

DOSAGE AND ADMINISTRATION

DISTRIBUTED BY:

MEIJER DISTRIBUTION, INC.

GRAND RAPIDS, MI 49544

WWW.MEIJER.COM

MADE IN KOREA